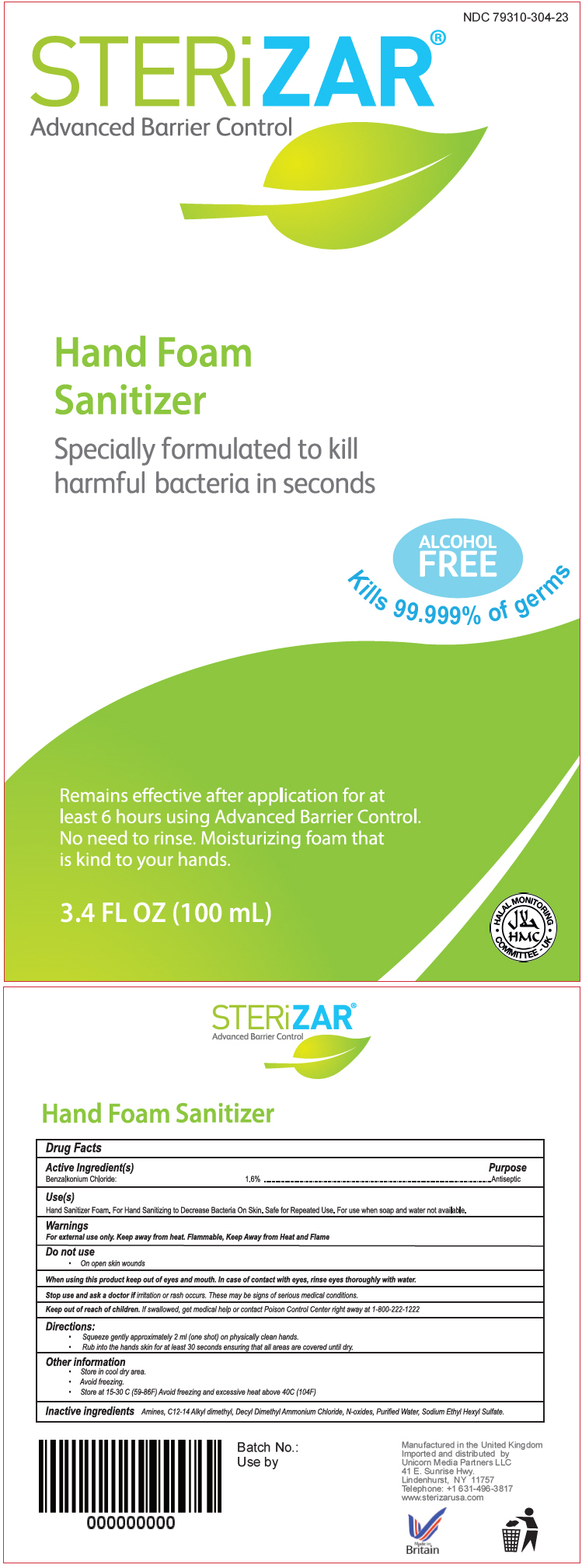 DRUG LABEL: STERiZAR 
NDC: 79310-304 | Form: SPRAY
Manufacturer: Unicorn Media Partners LLC
Category: otc | Type: HUMAN OTC DRUG LABEL
Date: 20201104

ACTIVE INGREDIENTS: Benzalkonium Chloride 16 mg/1 mL
INACTIVE INGREDIENTS: DIDECYLDIMONIUM CHLORIDE; SODIUM ETHASULFATE; WATER

STERiZAR®
Advanced Barrier Control

Drug Facts

Active Ingredient(s)

Benzalkonium Chloride 1.6 %

Purpose

Antiseptic

Use(s)

Hand Sanitizer Foam. For Hand Sanitizing to Decrease Bacteria On Skin. Safe for Repeated Use. For use when soap and water not available.

Warnings

For external use only. Keep away from heat. Flammable, Keep Away from Heat and Flame

Do not use

- On open skin wounds

When using this product keep out of eyes and mouth. In case of contact with eyes, rinse eyes thoroughly with water.

Stop use and ask a doctor if irritation or rush occurs These may be sign of serious medical conditions.

Keep out of reach of children. If swallowed, get medical help or contact Poison Control Center right away at 1-800-222-1222

Directions

- Squeeze gently approximately 2 ml (one shot) on physically clean hands.
- Rub into the hands skin for at least 30 second ensuring that all areas are covered until dry.

Other information

- Store in cool dry area.
- Avoid freezing
- Store at 15-30 C (59-86F) Avoid freezing and excessive heat above 40C (104F)

Inactive ingredients

Amines, C12-14 Alkyl dimethyl, Decyl Dimethyl Ammonium Chloride, N-oxides, Purified Water, Sodium Ethyl Hexyl Sulfate.

Imported and distributed by
Unicorn Media Partners LLC
41 E. Sunrise Hwy.
Lindenhurst, NY 11757

PRINCIPAL DISPLAY PANEL - 100 mL Bottle Label

NDC 79310-304-23

STERiZAR®
Advanced Barrier Control

Hand Foam
Sanitizer

Specially formulated to kill
harmful bacteria in seconds

ALCOHOL
FREE

Kills 99.999% of germs

Remains effective after application for at
least 6 hours using Advanced Barrier Control.
No need to rinse. Moisturizing foam that
is kind to your hands.

3.4 FL OZ (100 mL)

• HALAL MONITORING •
COMMITTEE - UK